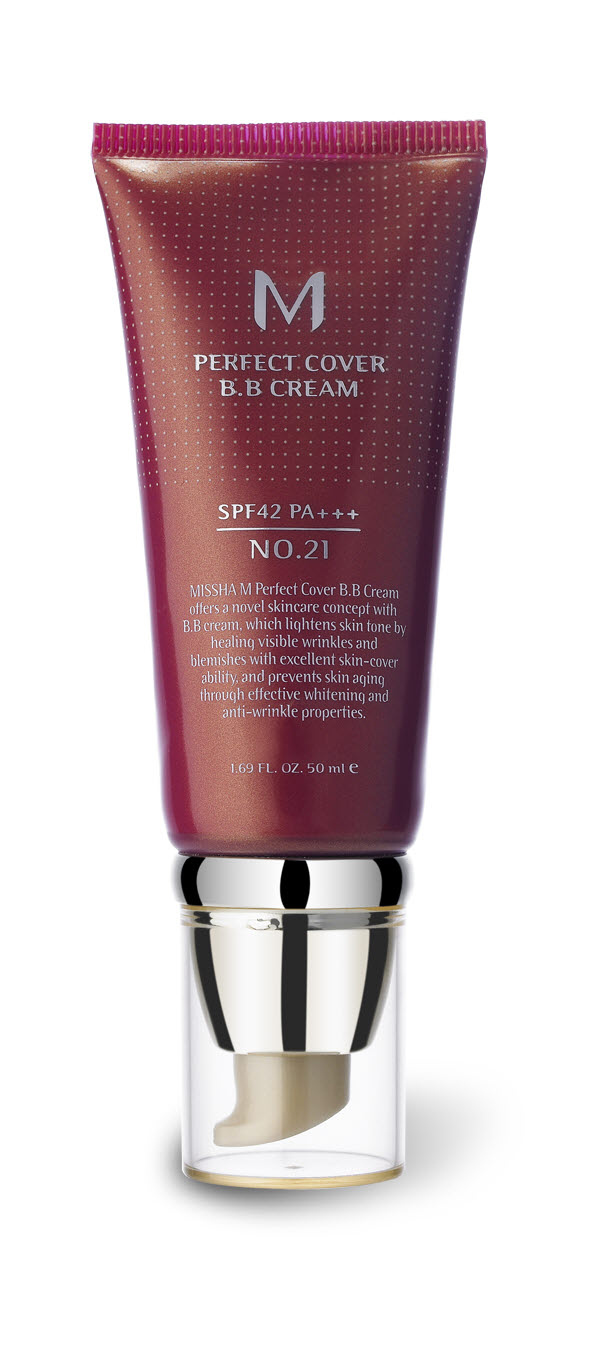 DRUG LABEL: MISSHA M PERFECT COVER BB
NDC: 13733-002 | Form: CREAM
Manufacturer: ABLE C&C CO., LTD.
Category: otc | Type: HUMAN OTC DRUG LABEL
Date: 20100518

ACTIVE INGREDIENTS: ZINC OXIDE 3.5 mL/50 mL

Drug Facts

Active Ingredient: ZINC OXIDE

Inactive Ingredients:
Water, Cyclopentasiloxane, Dimethicone/Vinyl Dimethicone Crosspolymer, Cetyl PEG/PPG-10/1 Dimethicone, Ethylhexyl Methoxycinnamate, Titanium Dioxide, Dimethicone, Caprylic/Capric Triglyceride, Butylene Glycol, PEG-10 Dimethicone, Arbutin, Triethanolamine, Iron Oxides, Magnesium Aluminum Silicate, Stearalkonium Hectorite, Methylparaben, Fragrance, Propylparaben, Hydrolyzed Collagen, Rosa Rubiginosa Seed Oil, Simmondsia Chinensis (Jojoba) Seed Oil, Squalane, Caviar Extract, Adenosine, Algae Extract, Macadamia Ternifolia Seed Oil, Fagus Sylvatica Bud Extract, Rosmarinus Officinalis (Rosemary) Leaf Extract, Sodium Hyaluronate, Ceramide 3, Chamomilla Recutita (Matricaria) Flower Extract

DESCRIPTION

Directions: After basic skin care, apply an appropriate amount along the skin texture and finish with powder. Do not need to apply Sun cream in addition.
Caution: For external use only. Do not swallow. Keep out of reach of children. Avoid contact with eyes.